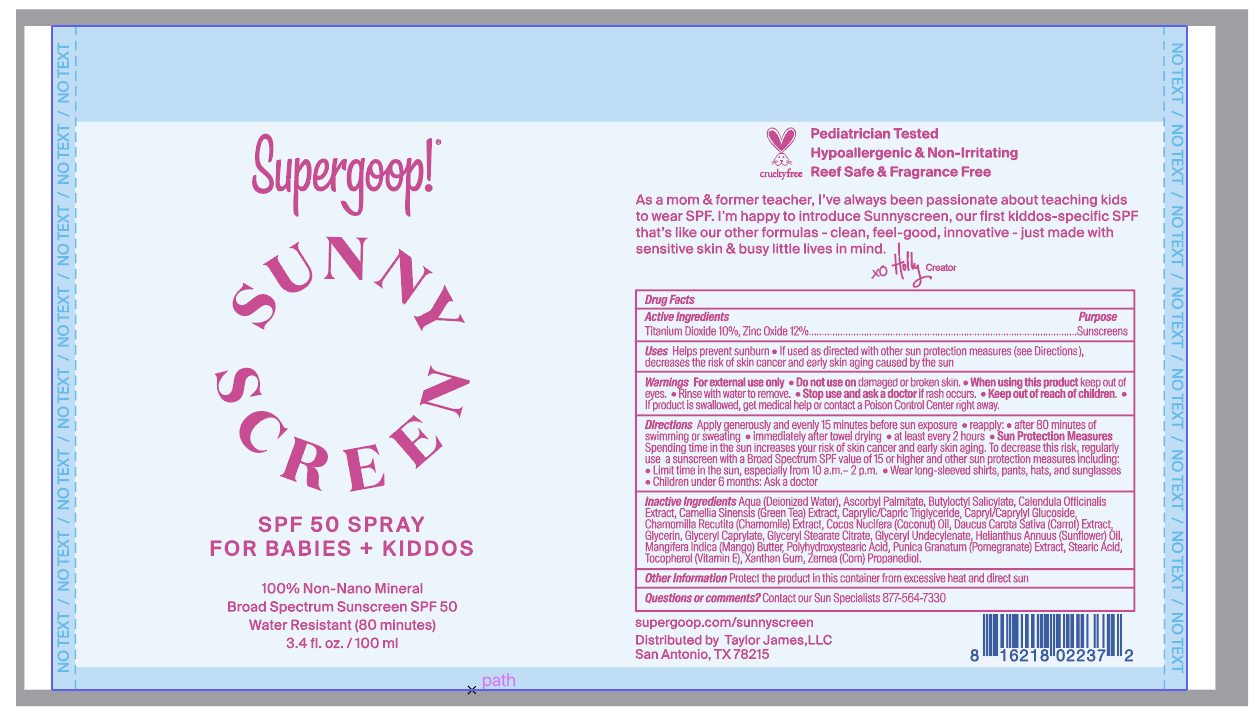 DRUG LABEL: Sunnyscreen SPF 50
NDC: 75936-252 | Form: SPRAY
Manufacturer: Supergoop, LLC
Category: otc | Type: HUMAN OTC DRUG LABEL
Date: 20241216

ACTIVE INGREDIENTS: TITANIUM DIOXIDE 10 g/100 mL; ZINC OXIDE 12 g/100 mL
INACTIVE INGREDIENTS: COCONUT OIL; WATER; ASCORBYL PALMITATE; GREEN TEA LEAF; GLYCERYL STEARATE CITRATE; TOCOPHEROL; CALENDULA OFFICINALIS FLOWER; MEDIUM-CHAIN TRIGLYCERIDES; GLYCERYL MONOCAPRYLATE; POLYHYDROXYSTEARIC ACID (2300 MW); STEARIC ACID; XANTHAN GUM; PROPANEDIOL; BUTYLOCTYL SALICYLATE; GLYCERYL 1-UNDECYLENATE; GLYCERIN; PUNICA GRANATUM ROOT BARK; MATRICARIA CHAMOMILLA

Sunnyscreen SPF 50 Spray for babies + Kiddos

Active Ingredient Purpose

Titanium Dioxide 10% Sunscreen

Zinc Oxide 12% Sunscreen

Uses

- Helps prevent sunburn
- If used as directed with other sun protection measures (see Directions), decreases the risk of skin cancer and early skin aging caused by the sun.

Keep out of reach of children

If product is swallowed, get medical help or contact a Poison Control Center right away.

Stop use and ask a doctor if rash occurs

Warnings

For external use only

Do not use on damaged or broken skin

When using this product, keep out of eyes. Rinse with water to remove.

Directions

- Apply generously and evenly 15 minutes before sun exposure
- Reapply:
- after 80 minutes of swimming or sweating • immediately after towel drying
- at least every 2 hours.
- Sun Protection Measures Spending time in the sun increases your risk of

skin cancer and early skin aging. To decrease this risk, regularly use a
sunscreen with a Broad Spectrum SPF value of 15 or higher and other sun
protection measures including: • limit your time in the sun, especially from 10
a.m. – 2 p.m. • wear long-sleeved shirts, pants, hats, and sunglasses

- Children under 6 months of age: ask a doctor.

Inactive Ingredients

Aqua (Deionized water), Ascorbyl Palmitate, Butyloctyl Salicylate, Calendula Officinalis Extract, Camellia Sinensis (Green Tea) Extract, Caprylic/Capric Triglyceride, Capryl/Caprylyl Glucoside, Chamomilla Recutita (Chamomile) Extract, Cocos Nucifera (Coconut) Oil, Daucus Carota Sativa (Carrot) Extract, Glycerin, Glyceryl Caprylate, Glyceryl Stearate Citrate, Glyceryl Undecylenate, Helianthus Annuus (Sunflower) Oil, Mangifera Indica (Mango) Butter, Polyhydroxystearic Acid, Punica Granatum (Pomegranate) Extract, Stearic Acid, Tocopherol (Vitamin E), Xanthan Gum, Zemea (Corn) Propanediol.

PACKAGE LABEL

Supergoop

Sunnyscreen SPF 50 spray for babies + kiddos

Broad Spectrum Sunscreen SPF 50

Water Resistant (80 minutes)

3.4 fl oz./100 ml